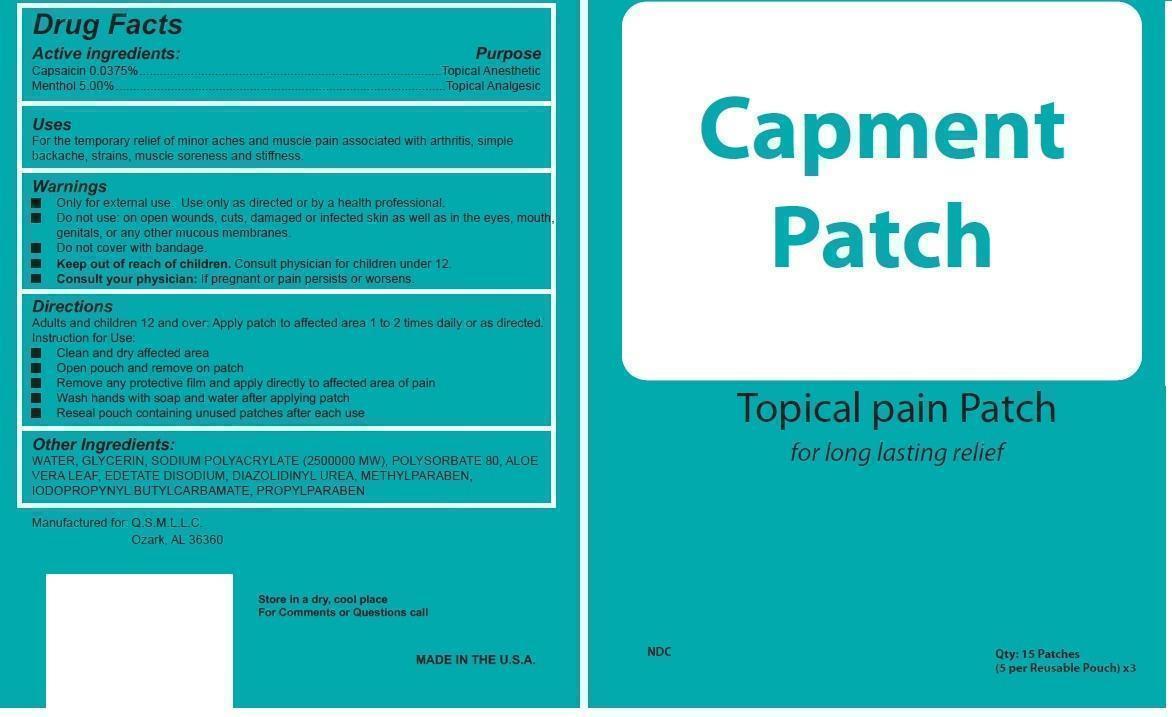 DRUG LABEL: Capment
NDC: 69650-002 | Form: PATCH
Manufacturer: Original Patch Company Inc
Category: prescription | Type: HUMAN PRESCRIPTION DRUG LABEL
Date: 20150331

ACTIVE INGREDIENTS: MENTHOL .04 1/100 g; CAPSAICIN .00375 1/100 g
INACTIVE INGREDIENTS: SILICON DIOXIDE; ACRYLIC ACID/SODIUM ACRYLATE COPOLYMER (1:1; 600 MPA.S AT 0.2%)

Capment

Active ingredients:

Capsaicin 0.0375%

Menthol 5.00%

Purpose

Topical Anesthetic

Topical Analgesic

Keep out of reach of children. Consult physician for children under 12.

Uses

For the temporary relief of minor aches and muscle pain associated with arthritis, simple backache, strains, muscle soreness and stiffness.

Warnings

- Only for external use. Use only as directed or by a health professional.
- Do not use: on open wounds, cuts, damaged or infected skin as well as in the eyes, mouth, genitals, or any other mucous membranes.
- Do not cover with bandage.
- Consult your physician: If pregnant or pain persists or worsens.

Directions

Adults and children 12 and over: Apply patch to affected area 1 to 2 times daily or as directed.

Instructions for Use:

- Clean and dry affected area
- Open pouch and remove on patch
- Remove any protective film and apply directly to affected area of pain
- Wash hands with soap and water after applying patch
- Reseal pouch containing unused patches after each use

Other Ingredients:

WATER, GLYCERIN, SODIUM POLYACRYLATE (2500000 MW), POLYSORBATE 80, ALOE VERA LEAF, EDETATE DISODIUM, DIAZOLIDINYL UREA, METHYLPARABEN, IODOPROPYNYL BUTYLCARBAMATE, PROPYLPARABEN

STORAGE AND HANDLING

Store in a dry, cool place